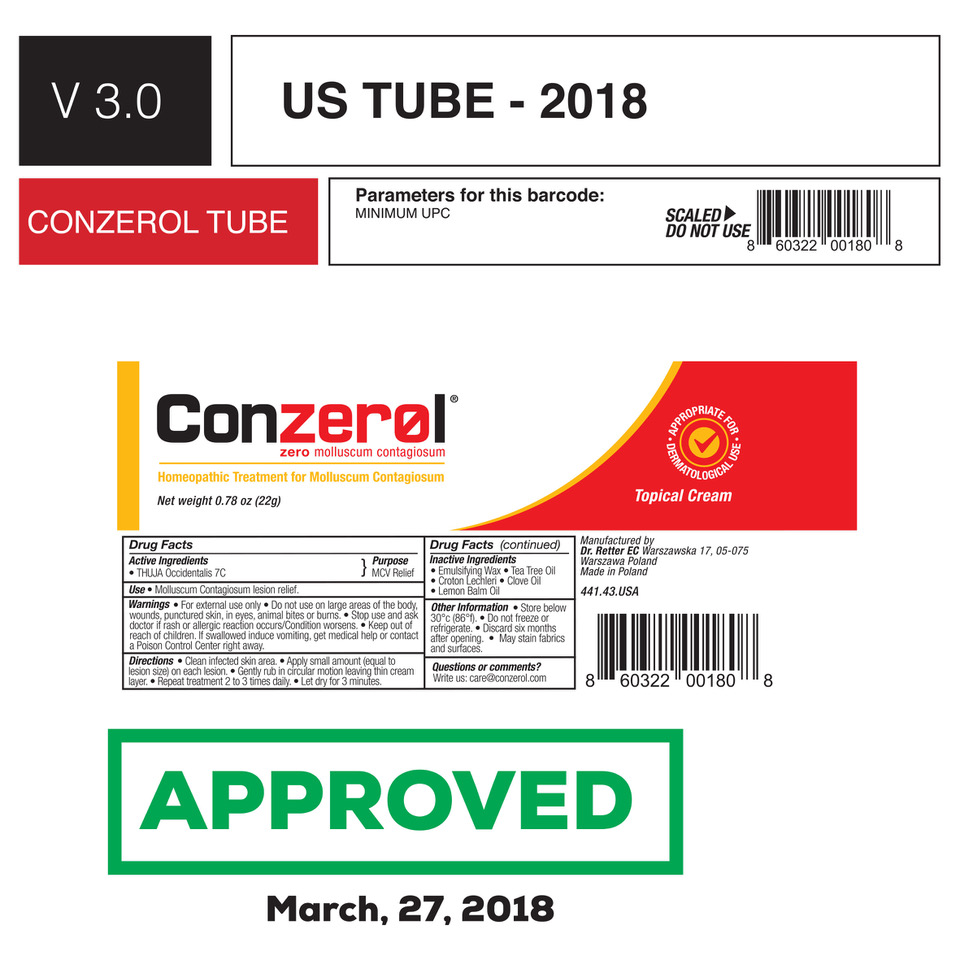 DRUG LABEL: Conzerol
NDC: 72383-000 | Form: CREAM
Manufacturer: Discovery Pharma Sp Z O O
Category: homeopathic | Type: HUMAN OTC DRUG LABEL
Date: 20200127

ACTIVE INGREDIENTS: CEDAR LEAF OIL 7 [hp_C]/1 g
INACTIVE INGREDIENTS: TEA TREE OIL; CROTON LECHLERI WHOLE; CLOVE OIL; LEMON BALM OIL; WHITE WAX

Conzerol

Active ingredients

Thuja Occidentalis 7C

Purpose

MCV Relief

Keep out of Reach of Children

Keep out of reach of children. If swallowed induce vomiting, get medical help or contact a Poison Control Center right away.

INDICATIONS AND USAGE

Molluscum Contagiosum lesion relief

Warnings

- For externa use only
- Do not use on large areas of the body, wounds, punctured skin, in the eyes, animal bited or burns
- Stop use and ask doctor if rash or allergic reaction occurs/Condition worsens
- Keep out of reach of children. If swallowed induce vomiting, get medical help or contact a Poison Control Center right away

Directions

- Clean infected skin area
- Apply small amount (equal to lesion size) on each lesion
- Gently run in circular motion leaving thin cream layer
- Repeat treatment 2 to 3 times daily
- Let dry for 3 minutes

Inactive Ingredients

Emulsifying Wax, Tea Tree Oil, Croton Lecleri, Clove Oil, Lemon Balm Oil